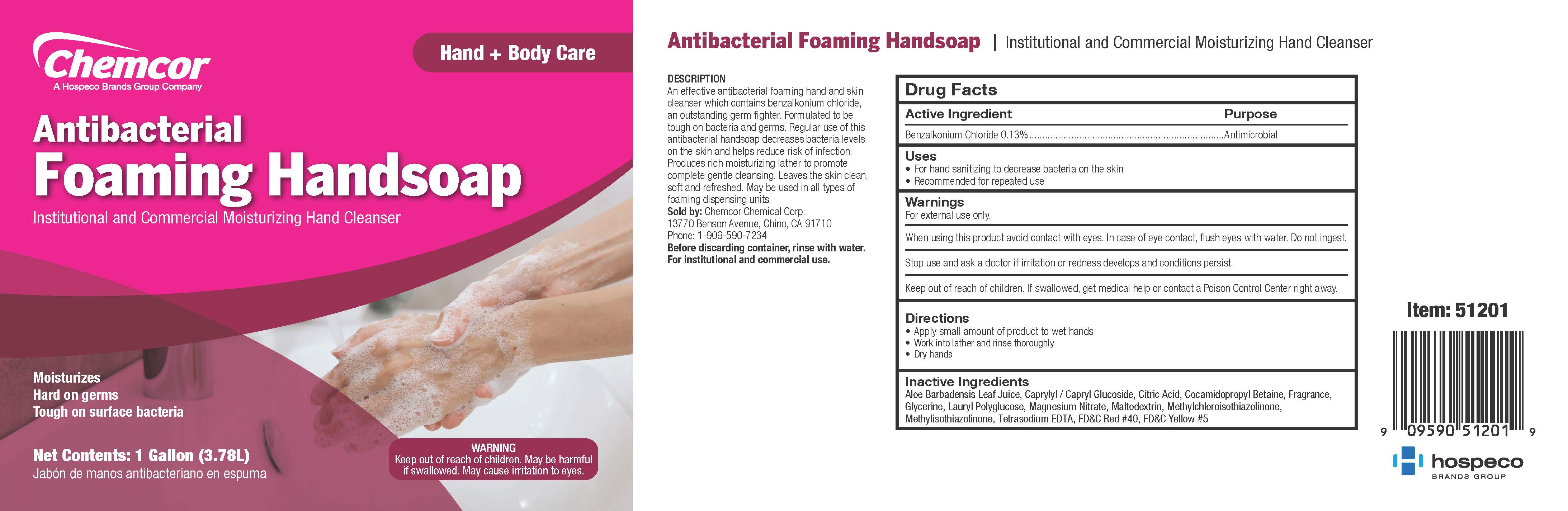 DRUG LABEL: Foaming Antibacterial Handsoap
NDC: 68041-512 | Form: LIQUID
Manufacturer: Chemcor Chemical Corporation
Category: otc | Type: HUMAN OTC DRUG LABEL
Date: 20251222

ACTIVE INGREDIENTS: BENZALKONIUM CHLORIDE 0.0013 mg/1 mL
INACTIVE INGREDIENTS: ALOE VERA LEAF; CAPRYLYL/CAPRYL OLIGOGLUCOSIDE; ANHYDROUS CITRIC ACID; COCAMIDOPROPYL BETAINE; GLYCERIN; LAURYL GLUCOSIDE; MAGNESIUM NITRATE; MALTODEXTRIN; METHYLCHLOROISOTHIAZOLINONE; METHYLISOTHIAZOLINONE; FD&C RED NO. 40; EDETATE SODIUM; WATER; FD&C YELLOW NO. 5

CHEMCOR Foaming Antibacterial Hand Soap

Active Ingredient

Benzalkonium Chloride 0.13%

Purpose

Antibacterial

Uses

- Antibacterial foaming hand cleaner.
- Use in daycare, hospitals, nursing homes, physician offices, dental offices and clinics.

Warnings

- For external use only.
- Avoid contact with eyes.
- If contact occurs, rinse thoroughly with water.
- Discontinue use if irritation to redness develops.
- If irritation persists for more than 72 hours, consult a physician.

- KEEP OUT OF REACH OF CHILDREN.
- If swallowed, get medical help or contact a Poison Control Center right away.

Directions

- Read the entire label before using this product.
- Ready to use without dilution.
- Dispense 2 pumps of product onto palm of hand and scrub thoroughly over all surfaces of both hands.
- Rinse with clean water and dry.

Inactive Ingredients

Water, Cocamidopropyl Betaine, Caprylyl Glucoside, Glycerine, Tetrasodium EDTA, Benzisothiazol, Methylisothiozol, Fragrance, Citric Acid, Aloe Vera, Yellow #5, Red #40

moisturizes
hard on germs
tough on surface bacteria

CHEMCOR

CHEMICAL CORP

CHINO, CA 91710

CHEMCORCHEMICAL.COM

WARNING
Keep out of reach of children.
May be harmful if swallowed.
May cause irritation to eyes.

institutional & commercial antibacterial hand cleanser

DESCRIPTION
An effective antibacterial foaming hand and skin cleanser which contains benzalkonium chloride, an outstanding germ fighter. Formulated to be tough on bacteria and germs. Regular use of this antibacterial handsoap decreases bacteria levels on the skin and helps reduce risk of infection. Produces rich moisturizing lather to promote complete gentle cleansing. Leaves the skin clean, soft and refreshed. May be used in all types of foaming dispensing units.

Before discarding container, rinse with water.
For institutional and commercial use.
Antes de descargar el contenedor, enjuague con agua.
Para uso institucional y comercial.